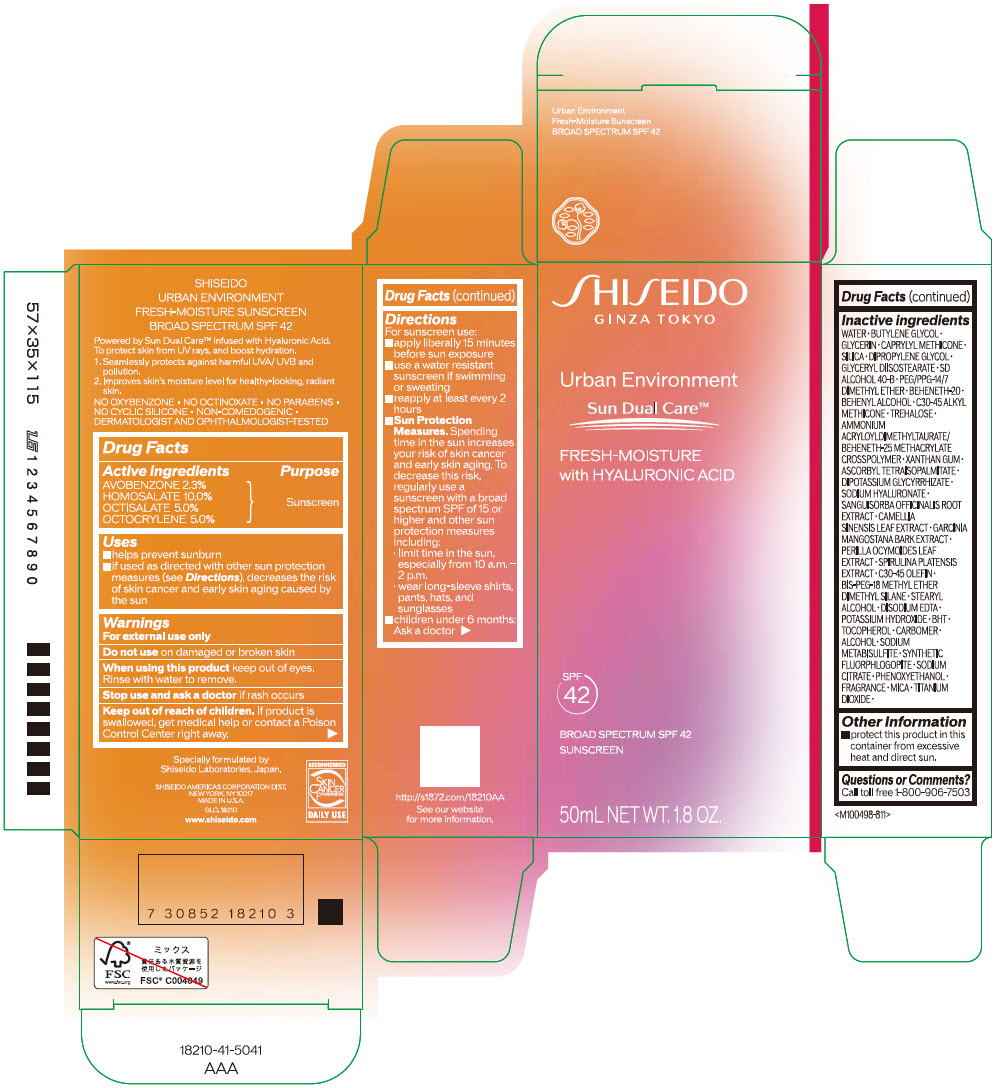 DRUG LABEL: SHISEIDO URBAN ENVIRONMENT FRESH-MOISTURE SUNSCREEN SPF 42
NDC: 58411-671 | Form: CREAM
Manufacturer: SHISEIDO AMERICAS CORPORATION
Category: otc | Type: HUMAN OTC DRUG LABEL
Date: 20260204

ACTIVE INGREDIENTS: AVOBENZONE 1.2 g/50 mL; HOMOSALATE 5.2 g/50 mL; OCTISALATE 2.6 g/50 mL; OCTOCRYLENE 2.6 g/50 mL
INACTIVE INGREDIENTS: WATER; BUTYLENE GLYCOL; GLYCERIN; CAPRYLYL TRISILOXANE; SILICON DIOXIDE; DIPROPYLENE GLYCOL; GLYCERYL DIISOSTEARATE; PEG/PPG-14/7 DIMETHYL ETHER; BEHENETH-20; DOCOSANOL; C30-45 ALKYL METHICONE; TREHALOSE; AMMONIUM ACRYLOYLDIMETHYLTAURATE/BEHENETH-25 METHACRYLATE CROSSPOLYMER (52000 MPA.S); XANTHAN GUM; ASCORBYL TETRAISOPALMITATE; GLYCYRRHIZINATE DIPOTASSIUM; HYALURONATE SODIUM; SANGUISORBA OFFICINALIS ROOT; GREEN TEA LEAF; GARCINIA MANGOSTANA BARK; PERILLA FRUTESCENS LEAF; C30-45 OLEFIN; BIS-PEG-18 METHYL ETHER DIMETHYL SILANE; STEARYL ALCOHOL; EDETATE DISODIUM; POTASSIUM HYDROXIDE; BUTYLATED HYDROXYTOLUENE; .ALPHA.-TOCOPHEROL; CARBOMER HOMOPOLYMER, UNSPECIFIED TYPE; ALCOHOL; SODIUM METABISULFITE; SODIUM CITRATE, UNSPECIFIED FORM; PHENOXYETHANOL; MICA; TITANIUM DIOXIDE

SHISEIDO URBAN ENVIRONMENT FRESH-MOISTURE SUNSCREEN SPF 42

Drug Facts

ACTIVE INGREDIENT

Active ingredients | Purpose
AVOBENZONE 2.3% | Sunscreen
HOMOSALATE 10.0% | Sunscreen
OCTISALATE 5.0% | Sunscreen
OCTOCRYLENE 5.0% | Sunscreen

Uses

- helps prevent sunburn
- if used as directed with other sun protection measures (see Directions), decreases the risk of skin cancer and early skin aging caused by the sun

Warnings

For external use only

Do not useon damaged or broken skin

WHEN USING

When using this productkeep out of eyes. Rinse with water to remove.

Stop use and ask a doctorif rash occurs.

Keep out of reach of children.If product is swallowed, get medical help or contact a Poison Control Center right away.

Directions

For sunscreen use:

- apply liberally 15 minutes before sun exposure
- use a water resistant sunscreen if swimming or sweating
- reapply at least every 2 hours
- Sun Protection Measures. Spending time in the sun increases your risk of skin cancer and early skin aging. To decrease this risk, regularly use a sunscreen with a broad spectrum SPF of 15 or higher and other un protection measures including:
  - limit time in the sun, especially from 10 a.m. – 2 p.m.
  - wear long-sleeve shirts, pants, hats, and sunglasses
- children under 6 months: Ask a doctor

Inactive Ingredients

WATER▪BUTYLENE GLYCOL▪GLYCERIN▪CAPRYLYL METHICONE▪SILICA▪DIPROPYLENE GLYCOL▪GLYCERYL DIISOSTEARATE▪SD ALCOHOL 40-B▪PEG/PPG-14/7 DIMETHYL ETHER▪BEHENETH-20▪BEHENYL ALCOHOL▪C30-45 ALKYL METHICONE▪TREHALOSE▪AMMONIUM ACRYLOYLDIMETHYLTAURATE/BEHENETH-25 METHACRYLATE CROSSPOLYMER▪XANTHAN GUM▪ASCORBYL TETRAISOPALMITATE▪DIPOTASSIUM GLYCYRRHIZATE▪SODIUM HYALURONATE▪SANGUISORBA OFFICINALIS ROOT EXTRACT▪CAMELLIA SINENSIS LEAF EXTRACT▪GARCINIA MANGOSTANA BARK EXTRACT▪PERILLA OCYMOIDES LEAF EXTRACT▪SPIRULINA PLATENSIS EXTRACT▪C30-45 OLEFIN▪BIS-PEG-18 METHYL ETHER DIMETHYL SILANE▪STEARYL ALCOHOL▪DISODIUM EDTA▪POTASSIUM HYDROXIDE▪BHT▪TOCOPHEROL▪CARBOMER▪ALCOHOL▪SODIUM METABISULFITE▪SYNTHETIC FLUORPHLOGOPITE▪SODIUM CITRATE▪PHENOXYETHANOL▪FRAGRANCE▪MICA▪TITANIUM DIOXIDE▪

Other information

- protect this product in this container from excessive heat and direct sun.

Questions or comments?

Call toll free 1-800-906-7503

PRINCIPAL DISPLAY PANEL - 50mL Tube Carton

SHISEIDO
GINZA TOKYO

Urban Environment
Sun Dual Care™

FRESH-MOISTURE
with HYALURONIC ACID

SPF
42

BROAD SPECTRUM SPF 42
SUNSCREEN

50mL NET WT. 1.8 OZ.